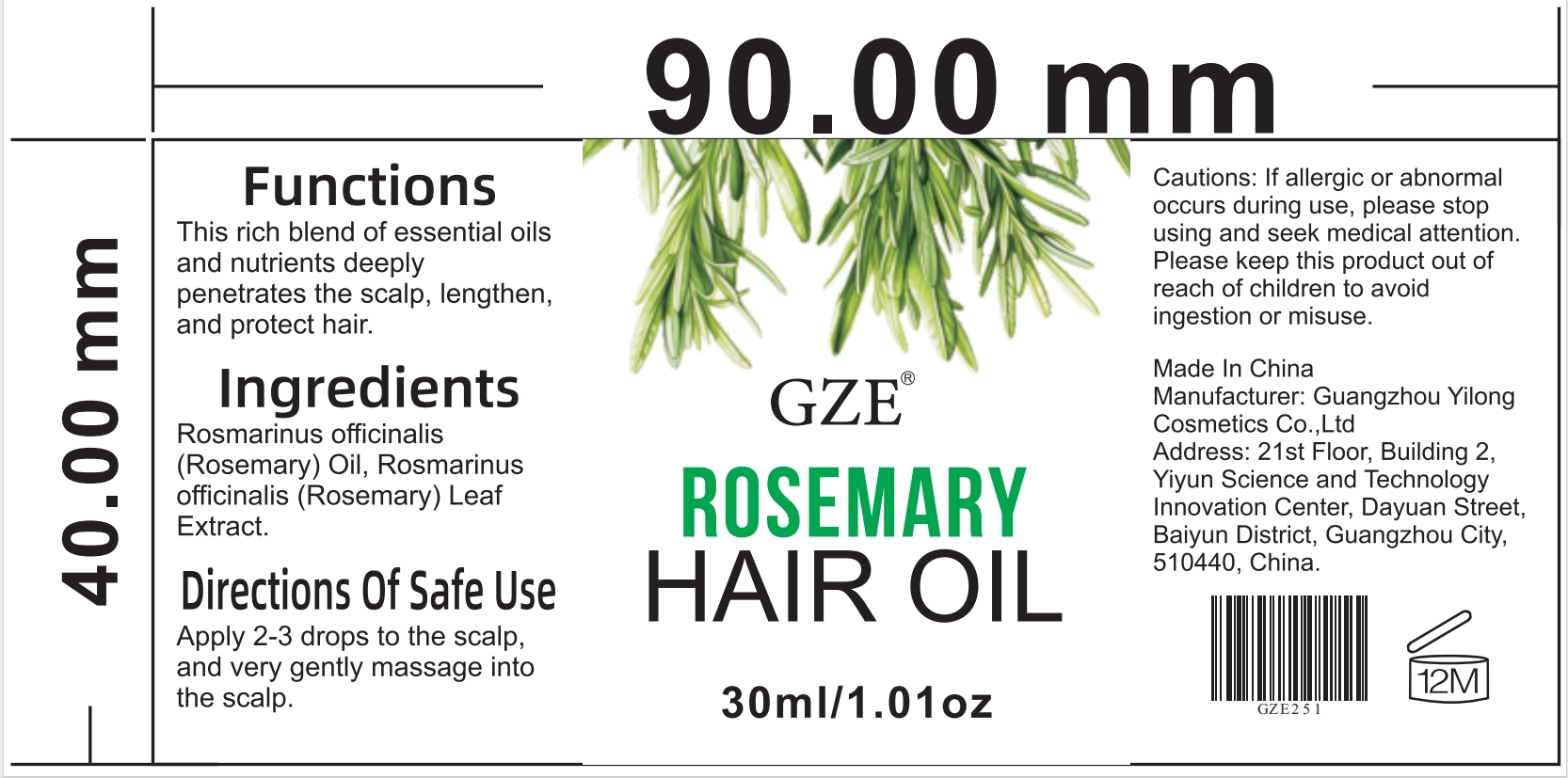 DRUG LABEL: GZE Rosemary Hair Oil
NDC: 74458-251 | Form: OIL
Manufacturer: Guangzhou Yilong Cosmetics Co., Ltd
Category: otc | Type: HUMAN OTC DRUG LABEL
Date: 20241009

ACTIVE INGREDIENTS: ROSEMARY OIL 99.9 g/100 mL
INACTIVE INGREDIENTS: ROSEMARY

GZE Rosemary Hair Oil

ACTIVE INGREDIENT

Rosmarinus officinalis (Rosemary) Oil

INACTIVE INGREDIENT

Rosmarinus officinalis (Rosemary) Leaf Extract.

PURPOSE

This rich blend of essential oils and nutrients deeply penetrates the scalp, lengthen, and protect hair.

INDICATIONS AND USAGE

Apply 2-3 drops to the scalp, and very gently massage into the scalp.

WARNINGS

For external use only.

Stop use and ask a doctor if rash occurs.

Do not use on damaged or broken skin.

When using this product keep out of eyes. Rinse with water to remove.

Keep out of reach of children. If swallowed, get medical help or contact a Poison Control Center right away.

DOSAGE AND ADMINISTRATION

Apply 2-3 drops to the scalp, and very gently massage into the scalp.